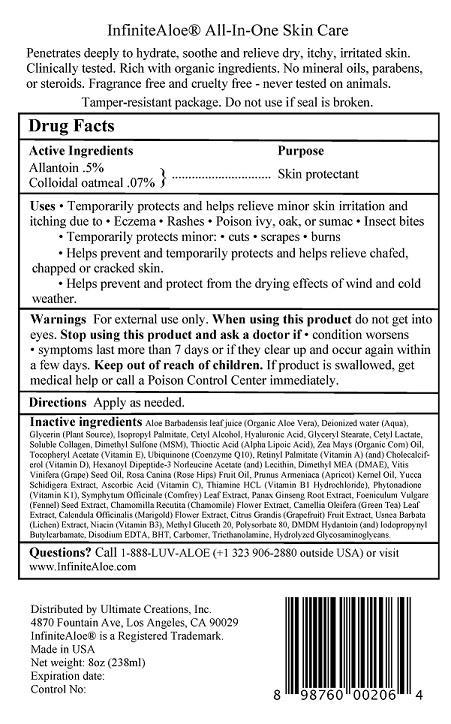 DRUG LABEL: INFINITE ALOE SKIN CARE
NDC: 69069-102 | Form: LOTION
Manufacturer: Economical Solutions, Inc. (DBA INFINITE ALOE)
Category: otc | Type: HUMAN OTC DRUG LABEL
Date: 20170526

ACTIVE INGREDIENTS: ALLANTOIN 0.5 g/100 mL; OATMEAL 0.07 g/100 mL
INACTIVE INGREDIENTS: ALOE VERA LEAF; WATER; GLYCERIN; ISOPROPYL PALMITATE; CETYL ALCOHOL; HYALURONIC ACID; GLYCERYL MONOSTEARATE; CETYL LACTATE; COLLAGEN, SOLUBLE, FISH SKIN; DIMETHYL SULFONE; THIOCTIC ACID, (+)-; CORN OIL; .ALPHA.-TOCOPHEROL ACETATE; UBIQUINONE Q2; VITAMIN A PALMITATE; CHOLECALCIFEROL; HEXANOYL DIPEPTIDE-3 NORLEUCINE ACETATE; LECITHIN, SOYBEAN; DEANOL; GRAPE SEED OIL; ROSA CANINA FRUIT OIL; APRICOT KERNEL OIL; YUCCA SCHIDIGERA; ASCORBIC ACID; THIAMINE HYDROCHLORIDE; PHYTONADIONE; COMFREY LEAF; PANAX GINSENG ROOT WATER; FENNEL SEED; CHAMOMILE; GREEN TEA LEAF; CALENDULA OFFICINALIS FLOWER; GRAPEFRUIT JUICE; USNEA BARBATA; NIACIN; METHYL GLUCETH-20; POLYSORBATE 80; DMDM HYDANTOIN; IODOPROPYNYL BUTYLCARBAMATE; EDETATE DISODIUM; BUTYLATED HYDROXYTOLUENE; CARBOMER 934; TROLAMINE; HYDROLYZED GLYCOSAMINOGLYCANS (BOVINE; 50000 MW)

ACTIVE INGREDIENTS

ALLANTOIN .5%

COLLOIDAL OATMEAL .07%

PURPOSE

SKIN PROTECTANT

Uses

Temporarily protects and helps relieve minor skin irritation and itching due to

- Eczema
- Rashes
- Poison ivy, oak, or sumac
- Insect bites

Temporarily protects minor:

- cuts
- scrapes
- burns
- Helps prevent and temporarily protects and helps relieve chafed,chapped or cracked skin.
- Helps prevent and protect from the drying effects of wind and cold weather.

WARNINGS

Warnings For external use only. When using this product do not get into eyes. Stop using this product and ask a doctor if

- condition worsens
- symptoms last more than 7 days or if they clear up and occur again within a few days.

Keep out of reach of children. If product is swallowed, get medical help or call a Poison Control Center immediately.

DIRECTIONS

APPLY AS NEEDED

INACTIVE INGREDIENT

Inactive ingredients Aloe Barbadensis leaf juice (Organic Aloe Vera), Deionized water (Aqua), Glycerin (Plant Source), Isopropyl Palmitate, Cetyl Alcohol, Hyaluronic Acid, Glyceryl Stearate, Cetyl Lactate, Soluble Collagen, Dimethyl Sulfone (MSM), Thioctic Acid (Alpha Lipoic Acid), Zea Mays (Organic Corn) Oil, Tocopheryl Acetate (Vitamin E), Ubiquinone (Coenzyme Q10), Retinyl Palmitate (Vitamin A) (and) Cholecalciferol
(Vitamin D), Hexanoyl Dipeptide-3 Norleucine Acetate (and) Lecithin, Dimethyl MEA (DMAE), Vitis Vinifera (Grape) Seed Oil, Rosa Canina (Rose Hips) Fruit Oil, Prunus Armeniaca (Apricot) Kernel Oil, Yucca Schidigera Extract, Ascorbic Acid (Vitamin C), Thiamine HCL (Vitamin B1 Hydrochloride), Phytonadione (Vitamin K1), Symphytum Officinale (Comfrey) Leaf Extract, Panax Ginseng Root Extract, Foeniculum Vulgare
(Fennel) Seed Extract, Chamomilla Recutita (Chamomile) Flower Extract, Camellia Oleifera (Green Tea) Leaf Extract, Calendula Officinalis (Marigold) Flower Extract, Citrus Grandis (Grapefruit) Fruit Extract, Usnea Barbata (Lichen) Extract, Niacin (Vitamin B3), Methyl Gluceth 20, Polysorbate 80, DMDM Hydantoin (and) Iodopropynyl Butylcarbamate, Disodium EDTA, BHT, Carbomer, Triethanolamine, Hydrolyzed Glycosaminoglycans.

QUESTIONS

Questions? Call 1-888-LUV-ALOE (+1 323 906-2880 outside USA) or visit www.InfiniteAloe.com